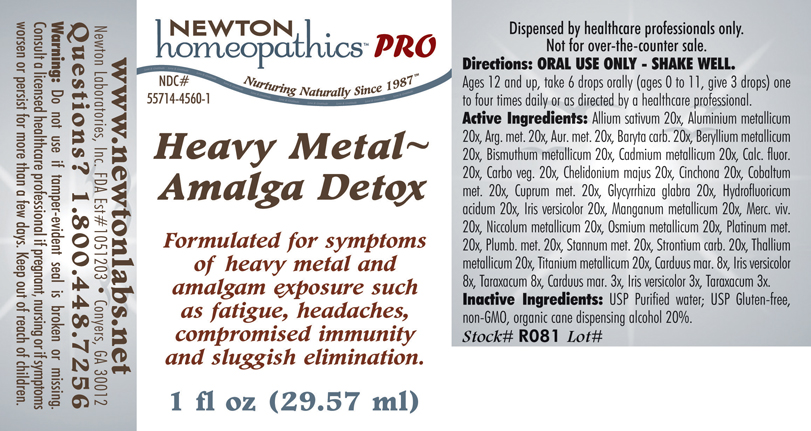 DRUG LABEL: Heavy Metal Amalga Detox 
NDC: 55714-4560 | Form: LIQUID
Manufacturer: Newton Laboratories, Inc.
Category: homeopathic | Type: HUMAN PRESCRIPTION DRUG LABEL
Date: 20110601

ACTIVE INGREDIENTS: Garlic 20 [hp_X]/1 mL; Aluminum 20 [hp_X]/1 mL; Silver 20 [hp_X]/1 mL; Gold 20 [hp_X]/1 mL; Barium Carbonate 20 [hp_X]/1 mL; Beryllium 20 [hp_X]/1 mL; Bismuth 20 [hp_X]/1 mL; Cadmium 20 [hp_X]/1 mL; Calcium Fluoride 20 [hp_X]/1 mL; Activated Charcoal 20 [hp_X]/1 mL; Chelidonium Majus 20 [hp_X]/1 mL; Cinchona Officinalis Bark 20 [hp_X]/1 mL; Cobalt 20 [hp_X]/1 mL; Copper 20 [hp_X]/1 mL; Glycyrrhiza Glabra 20 [hp_X]/1 mL; Hydrofluoric Acid 20 [hp_X]/1 mL; Iris Versicolor Root 20 [hp_X]/1 mL; Manganese 20 [hp_X]/1 mL; Mercury 20 [hp_X]/1 mL; Nickel 20 [hp_X]/1 mL; Osmium 20 [hp_X]/1 mL; Platinum 20 [hp_X]/1 mL; Lead 20 [hp_X]/1 mL; Tin 20 [hp_X]/1 mL; Strontium Carbonate 20 [hp_X]/1 mL; Thallium 20 [hp_X]/1 mL; Titanium 20 [hp_X]/1 mL; Silybum Marianum Seed 8 [hp_X]/1 mL; Iris Versicolor Root 8 [hp_X]/1 mL; Taraxacum Officinale 8 [hp_X]/1 mL; Silybum Marianum Seed 3 [hp_X]/1 mL; Iris Versicolor Root 3 [hp_X]/1 mL; Taraxacum Officinale 3 [hp_X]/1 mL
INACTIVE INGREDIENTS: Alcohol

Heavy Metal Amalga Detox

PRODUCT NAME & INDICATIONS SECTION

HEAVY METAL AMALGA DETOX Formulated for symptoms of heavy metal and amalgam exposure such as fatigue, headaches, compromised immunity and sluggish elimination.

DIRECTION SECTION

Directions: ORAL USE ONLY - SHAKE WELL. Ages 12 and up, take 6 drops orally (ages 0 to 11, give 3 drops) one to four times daily or as directed by a healthcare professional.

ACTIVE INGREDIENT SECTION

Allium sativum 20x, Aluminium metallicum 20x, Arg. met. 20x, Aur. met. 20x, Baryta carb. 20x, Beryllium metallicum 20x, Bismuthum metallicum 20x, Cadmium metallicum 20x, Calc. fluor. 20x, Carbo veg. 20x, Chelidonium majus 20x, Cinchona 20x, Cobaltum met. 20x, Cuprum met. 20x, Glycyrrhiza glabra 20x, Hydrofluoricum acidum 20x, Iris versicolor 20x, Manganum metallicum 20x, Merc. viv. 20x, Niccolum metallicum 20x, Osmium metallicum 20x, Platinum met. 20x, Plumb. met. 20x, Stannum met. 20x, Strontium carb. 20x, Thallium metallicum 20x, Titanium metallicum 20x, Carduus mar. 8x, Iris versicolor 8x, Taraxacum 8x, Carduus mar. 3x, Iris versicolor 3x, Taraxacum 3x.

PURPOSE SECTION

Formulated for symptoms of heavy metal and amalgam exposure such as fatigue, headaches, compromised immunity and sluggish elimination.

INACTIVE INGREDIENT SECTION

Inactive Ingredients: USP Purified Water; USP Gluten-free, non-GMO, organic cane dispensing alcohol 20%.

QUESTIONS? SECTION

www.newtonlabs.net Newton Laboratories, Inc. FDA Est # 1051203 - Conyers, GA 30012
Questions? 1.800.448.7256

WARNINGS SECTION

Warning: Do not use if tamper - evident seal is broken or missing. Consult a licensed healthcare professional if pregnant, nursing or if symptoms worsen or persist for more than a few days. Keep out of reach of children.

OTC - PREGNANCY OR BREAST FEEDING SECTION

Consult a licensed healthcare professional if pregnant or nursing or if symptoms worsen or persist for more than a few days.

OTC - KEEP OUT OF REACH OF CHILDREN SECTION

Keep out of reach of children.